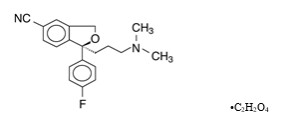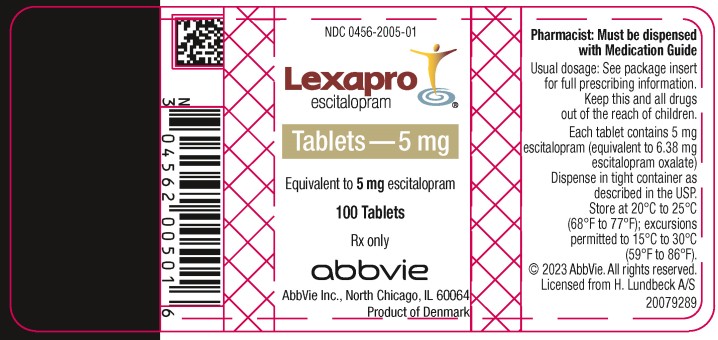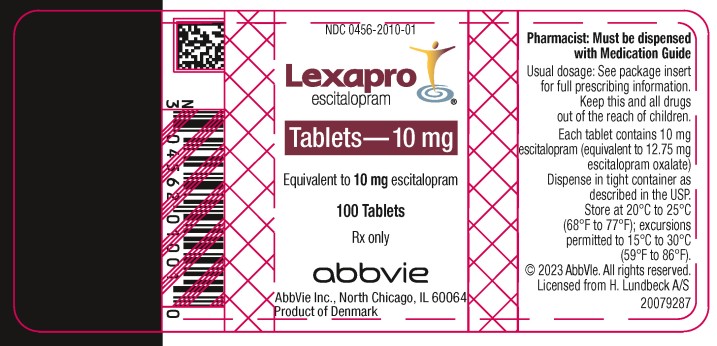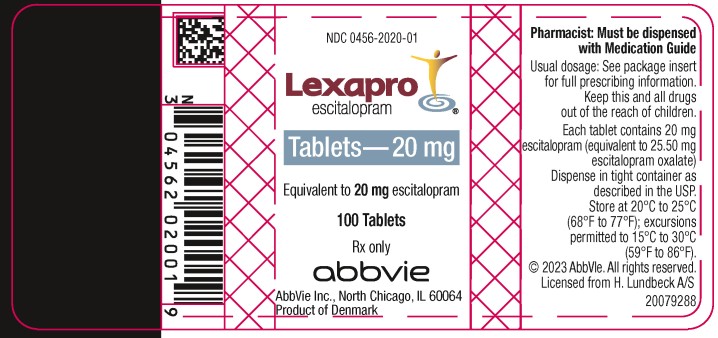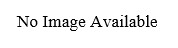 DRUG LABEL: Lexapro
NDC: 0456-2005 | Form: TABLET, FILM COATED
Manufacturer: Allergan, Inc.
Category: prescription | Type: HUMAN PRESCRIPTION DRUG LABEL
Date: 20231001

ACTIVE INGREDIENTS: ESCITALOPRAM OXALATE 5 mg/1 1
INACTIVE INGREDIENTS: TALC; CROSCARMELLOSE SODIUM; CELLULOSE, MICROCRYSTALLINE; SILICON DIOXIDE; MAGNESIUM STEARATE; HYPROMELLOSES; TITANIUM DIOXIDE; POLYETHYLENE GLYCOL, UNSPECIFIED

HIGHLIGHTS OF PRESCRIBING INFORMATION

These highlights do not include all the information needed to use LEXAPRO safely and effectively. See full prescribing information for LEXAPRO.
Lexapro® (escitalopram) tablets, for oral use
Lexapro® (escitalopram) oral solution
Initial U.S. Approval: 2002

RECENT MAJOR CHANGES

Indications (1) | 5/2023
Dosage and Administration (2.2, 2.3, 2.5) Dosage and Administration, Use of Lexapro with Other MAOIs such as Linezolid or Methylene Blue (2.7) - Removed | 5/2023 5/2023
Warnings and Precautions (5.2, 5.7) | 8/2023

WARNING: SUICIDAL THOUGHTS AND BEHAVIORS

See full prescribing information for complete boxed warning.

Increased risk of suicidal thoughts and behavior in pediatric and young adult patients taking antidepressants. Closely monitor all antidepressant-treated patients for clinical worsening and emergence of suicidal thoughts and behaviors (5.1). Lexapro is not approved for use in pediatric patients less than 7 years of age (8.4).

1 INDICATIONS AND USAGE

Lexapro is a selective serotonin reuptake inhibitor (SSRI) indicated for the:

- treatment of major depressive disorder (MDD) in adults and pediatric patients 12 years of age and older (1)
- treatment of generalized anxiety disorder (GAD) in adults and pediatric patients 7 years and older (1)

2 DOSAGE AND ADMINISTRATION

Indication and Population | Recommended Dosage
MDD in Adults (2.1) | Initial: 10 mg once daily Recommended: 10 mg once daily Maximum: 20 mg once daily
MDD in Pediatric Patients 12 years and older (2.1) | Initial: 10 mg once daily Recommended: 10 mg once daily Maximum: 20 mg once daily
GAD in Adults (2.2) | Initial: 10 mg once daily Recommended: 10 mg once daily Maximum: 20 mg once daily
GAD in Pediatric Patients 7 years and older (2.2) | Initial: 10 mg once daily Recommended: 10 mg once daily Maximum: 20 mg once daily

- No additional benefits were seen at 20 mg once daily (2.1)
- Administer once daily, morning or evening, with or without food (2.3)
- Elderly patients: recommended dosage is 10 mg once daily (2.4)
- Hepatic impairment: recommended dosage is 10 mg once daily (2.4, 8.6)
- When discontinuing Lexapro, reduce dose gradually whenever possible (2.5)

3 DOSAGE FORMS AND STRENGTHS

- Tablets: 5 mg, 10 mg (scored), and 20 mg (scored)
- Oral solution: 1 mg per mL (not currently being marketed)

4 CONTRAINDICATIONS

- Do not use MAOIs intended to treat psychiatric disorders with Lexapro or within 14 days of stopping treatment with Lexapro. Do not use Lexapro within 14 days of stopping an MAOI intended to treat psychiatric disorders. In addition, do not start Lexapro in a patient who is being treated with linezolid or intravenous methylene blue (4)
- Concomitant use of pimozide (4)
- Known hypersensitivity to escitalopram or citalopram or any of the inactive ingredients (4)

5 WARNINGS AND PRECAUTIONS

- Serotonin Syndrome: Increased risk when co-administered with other serotonergic agents but also when taken alone. If it occurs, discontinue Lexapro and serotonergic agents and initiate supportive treatment (4, 5.2)
- Discontinuation syndrome: When discontinuing Lexapro, reduce dosage gradually whenever possible, and monitor for discontinuation symptoms (5.3)
- Seizures: Use with caution in patients with a history of seizure (5.4)
- Activation of Mania/Hypomania: Screen patients for bipolar disorder (5.5)
- Hyponatremia: Can occur in association with syndrome of inappropriate antidiuretic hormone secretion (5.6)
- Increased Risk of Bleeding: Concomitant use of nonsteroidal anti-inflammatory drugs, aspirin, other antiplatelet drugs, warfarin and other drugs that affect coagulation may increase risk (5.7)
- Interference with Cognitive and Motor Performance: Use caution when operating machinery (5.8)
- Angle Closure Glaucoma: Angle closure glaucoma has occurred in patients with untreated anatomically narrow angles treated with antidepressants (5.9)
- Use in Patients with Concomitant Illness: Use caution in patients with diseases or conditions that produce altered metabolism or hemodynamic responses (5.10)
- Sexual Dysfunction: Lexapro may cause symptoms of sexual dysfunction (5.11)

6 ADVERSE REACTIONS

Most commonly observed adverse reactions (incidence ≥ 5% and at least twice the incidence of placebo patients) are: insomnia, ejaculation disorder (primarily ejaculatory delay), nausea, sweating increased, fatigue and somnolence, decreased libido, and anorgasmia (6.1)

To report SUSPECTED ADVERSE REACTIONS, contact AbbVie at 1-800- 678-1605, or FDA at 1-800-FDA-1088 or www.fda.gov/medwatch.

7 DRUG INTERACTIONS

- Concomitant use with SSRIs, SNRIs or Tryptophan is not recommended (7)
- Use caution when concomitant use with drugs that affect Hemostasis (NSAIDs, Aspirin, Warfarin) (7)

8 USE IN SPECIFIC POPULATIONS

- Pregnancy: SSRI use, particularly later in pregnancy, may increase the risk for persistent pulmonary hypertension and symptoms of poor adaptation (respiratory distress, temperature instability, feeding difficulties, hypotonia, tremor, irritability) in the neonate (8.1)

FULL PRESCRIBING INFORMATION

WARNING: SUICIDAL THOUGHTS AND BEHAVIORS

Antidepressants increased the risk of suicidal thoughts and behaviors in pediatric and young adult patients in short-term studies. Closely monitor all antidepressant-treated patients for clinical worsening, and for emergence of suicidal thoughts and behaviors [see Warnings and Precautions (5.1)]. Lexapro is not approved for use in pediatric patients less than 7 years of age [see Use in Specific Populations (8.4)].

1 INDICATIONS AND USAGE

Lexapro is indicated for the treatment of:

• major depressive disorder (MDD) in adults and pediatric patients 12 years of age and older.

• generalized anxiety disorder (GAD) in adults and pediatric patients 7 years of age and older.

2 DOSAGE AND ADMINISTRATION

2.1 Major Depressive Disorder

Adults

The recommended dosage of Lexapro in adults is 10 mg once daily. A fixed-dose trial of Lexapro demonstrated the effectiveness of both 10 mg and 20 mg of Lexapro, but failed to demonstrate a greater benefit of 20 mg over 10 mg [see Clinical Studies (14.1)]. Depending on clinical response and tolerability, dosage may be increased to the maximum recommended dosage of 20 mg once daily at an interval of no less than 1 week.

Pediatric Patients 12 years of age and older

The recommended dosage of Lexapro in pediatric patients 12 years of age and older is 10 mg once daily. Depending on clinical response and tolerability, dosage may be increased to the maximum recommended dosage of 20 mg once daily at an interval of no less than 3 weeks.

2.2 Generalized Anxiety Disorder

Adults

The recommended starting dosage of Lexapro in adults is 10 mg once daily. Depending on clinical response and tolerability, dosage may be increased to the maximum recommended dosage of 20 mg once daily at an interval of no less than 1 week.

Pediatric Patients 7 years of age and older

The recommended starting dosage of Lexapro for pediatric patients ages 7 years of age and older is 10 mg once daily. Depending on clinical response and tolerability, dosage may be increased to the maximum recommended dosage of 20 mg once daily at an interval of no less than 2 weeks.

2.3 Administration Information

Administer Lexapro orally once daily, in the morning or evening, with or without food.

2.4 Screen for Bipolar Disorder Prior to Starting Lexapro

Prior to initiating treatment with Lexapro or another antidepressant, screen patients for a personal family history of bipolar disorder, mania, or hypomania [see Warnings and Precautions (5.5)].

2.5 Recommended Dosage for Specific Populations

The recommended dosage for most elderly patients and patients with hepatic impairment is 10 mg once daily [see Use in Specific Populations (8.5, 8.6)].

The recommended dosage for Lexapro in adults with a creatinine clearance less than 20 mL/minute has not been determined. No dosage adjustment is necessary for patients with mild or moderate renal impairment [see Use in Specific Populations (8.7)].

2.6 Discontinuation of Treatment with Lexapro

Symptoms associated with discontinuation of Lexapro and other SSRIs and SNRIs have been reported [see Warnings and Precautions (5.3)]. Patients should be monitored for these symptoms when discontinuing treatment. A gradual reduction in the dose rather than abrupt cessation is recommended whenever possible. If intolerable symptoms occur following a decrease in the dose or upon discontinuation of treatment, then resuming the previously prescribed dose may be considered. Subsequently, the physician may continue decreasing the dose but at a more gradual rate.

2.7 Switching Patients to or from a Monoamine Oxidase Inhibitor (MAOI) Antidepressant

At least 14 days should elapse between discontinuation of an MAOI intended to treat psychiatric disorders and initiation of therapy with Lexapro. Conversely, at least 14 days should be allowed after stopping Lexapro before starting an MAOI intended to treat psychiatric disorders [see Contraindications (4)].

3 DOSAGE FORMS AND STRENGTHS

Tablets

5 mg: White to off-white, round, non-scored, film-coated. Imprint "FL" on one side of the tablet and "5" on the other side.

10 mg: White to off-white, round, scored, film-coated. Imprint on scored side with "F" on the left side and "L" on the right side. Imprint on the non-scored side with "10".

20 mg: White to off-white, round, scored, film-coated. Imprint on scored side with "F" on the left side and "L" on the right side. Imprint on the non-scored side with "20".

Oral Solution

1 mg/mL: Clear, colorless to opalescent liquid, peppermint flavor (not currently being marketed).

4 CONTRAINDICATIONS

Lexapro is contraindicated in patients:

- taking MAOIs with Lexapro or within 14 days of stopping treatment with Lexapro because of an increased risk of serotonin syndrome. The use of Lexapro within 14 days of stopping an MAOI intended to treat psychiatric disorders is also contraindicated [see Dosage and Administration (2.7) and Warnings and Precautions (5.2)]. Starting Lexapro in a patient who is being treated with MAOIs such as linezolid or intravenous methylene blue is also contraindicated because of an increased risk of serotonin syndrome [see Dosage and Administration (2.6) and Warnings and Precautions (5.2)].
- taking pimozide [see Drug Interactions (7)].
- with a hypersensitivity to escitalopram or citalopram or any of the inactive ingredients in Lexapro.

5 WARNINGS AND PRECAUTIONS

5.1 Suicidal Thoughts and Behaviors in Adolescents and Young Adults

In pooled analyses of placebo-controlled trials of antidepressant drugs (SSRIs and other antidepressant classes) that included approximately 77,000 adult patients and 4,500 pediatric patients, the incidence of suicidal thoughts and behaviors in the antidepressant-treated patients age 24 years and younger was greater than in placebo-treated patients. There was considerable variation in risk of suicidal thoughts and behaviors among drugs, but there was an increased risk identified in young patients for most drugs studied. There were differences in absolute risk of suicidal thoughts and behaviors across the different indications, with the highest incidence in patients with MDD. The drug-placebo differences in the number of cases of suicidal thoughts and behaviors per 1000 patients treated are provided in Table 1.

Table 1: Risk Differences of the Number of Patients of Suicidal Thoughts and Behaviors in the Pooled Placebo-Controlled Trials of Antidepressants in Pediatric and Adult Patients
Age Range | Drug-Placebo Difference in Number of Patients of Suicidal Thoughts and Behaviors per 1000 Patients Treated
 | Increases Compared to Placebo
<18 years old | 14 additional patients
18 to 24 years old | 5 additional patients
 | Decreases Compared to Placebo
25 to 64 years old | 1 fewer patient
≥65 years old | 6 fewer patients

It is unknown whether the risk of suicidal thoughts and behaviors in children, adolescents, and young adults extends to longer-term use, i.e., beyond four months. However, there is substantial evidence from placebo-controlled maintenance trials in adults with MDD that antidepressants delay the recurrence of depression and that depression itself is a risk factor for suicidal thoughts and behaviors.

Monitor all antidepressant-treated patients for any indication for clinical worsening and emergence of suicidal thoughts and behaviors, especially during the initial few months of drug therapy, and at times of dosage changes. Counsel family members or caregivers of patients to monitor for changes in behavior and to alert the healthcare provider. Consider changing the therapeutic regimen, including possibly discontinuing Lexapro, in patients whose depression is persistently worse, or who are experiencing emergent suicidal thoughts or behaviors.

5.2 Serotonin Syndrome

SSRIs, including Lexapro, can precipitate serotonin syndrome, a potentially life-threatening condition. The risk is increased with concomitant use of other serotonergic drugs (including triptans, tricyclic antidepressants, fentanyl, meperidine, methadone, lithium, tramadol, tryptophan, buspirone, amphetamines, and St. John’s Wort) and with drugs that impair metabolism of serotonin, i.e., MAOIs [see Contraindications (4) and Drug Interactions (7)].

Serotonin syndrome symptoms may include mental status changes (e.g., agitation, hallucinations, delirium, and coma), autonomic instability (e.g., tachycardia, labile blood pressure, dizziness, diaphoresis, flushing, hyperthermia), neuromuscular symptoms (e.g., tremor, rigidity, myoclonus, hyperreflexia, incoordination) seizures, and/or gastrointestinal symptoms (e.g., nausea, vomiting, diarrhea).

The concomitant use of Lexapro with MAOIs is contraindicated. In addition, do not initiate Lexapro in a patient who is being treated with MAOIs such as linezolid or intravenous methylene blue. No reports involved the administration of methylene blue by other routes (such as oral tablets or local tissue injection). If it is necessary to initiate treatment with an MAOI such as linezolid or intravenous methylene blue in a patient taking Lexapro, discontinue Lexapro before initiating treatment with the MAOI [see Contraindications (4) and Dosage and Administration (2.7)].

Monitor all patients taking Lexapro for the emergence of serotonin syndrome. Discontinue treatment with Lexapro and any concomitant serotonergic agents immediately if the above symptoms occur, and initiate supportive symptomatic treatment. If concomitant use of Lexapro with other serotonergic drugs is clinically warranted, inform patients of the increased risk for serotonin syndrome and monitor for symptoms.

5.3 Discontinuation Syndrome

During marketing of Lexapro and other SSRIs, there have been spontaneous reports of adverse reactions occurring upon discontinuation of these drugs, particularly when abrupt, including the following: dysphoric mood, irritability, agitation, dizziness, sensory disturbances (e.g., paresthesias such as electric shock sensations), anxiety, confusion, headache, lethargy, emotional lability, insomnia, and hypomania. While these events are generally self-limiting, there have been reports of serious discontinuation symptoms.

Monitor for these symptoms when discontinuing treatment with Lexapro. A gradual reduction in the dose rather than abrupt cessation is recommended whenever possible. If intolerable symptoms occur following a decrease in the dose or upon discontinuation of treatment, then resuming the previously prescribed dose may be considered. Subsequently, the physician may continue decreasing the dose but at a more gradual rate [see Dosage and Administration (2.6)].

5.4 Seizures

Although anticonvulsant effects of racemic citalopram have been observed in animal studies, Lexapro has not been systematically evaluated in patients with a seizure disorder. These patients were excluded from clinical studies during the product's premarketing testing. In clinical trials of Lexapro, cases of convulsion have been reported in association with Lexapro treatment. Like other drugs effective in the treatment of major depressive disorder, Lexapro should be introduced with care in patients with a history of seizure disorder.

5.5 Activation of Mania or Hypomania

In patients with bipolar disorder, treating a depressive episode with Lexapro or another antidepressant may precipitate a mixed/manic episode. In placebo-controlled trials of Lexapro in major depressive disorder, activation of mania/hypomania was reported in one (0.1%) of 715 patients treated with Lexapro and in none of the 592 patients treated with placebo. One additional case of hypomania has been reported in association with Lexapro treatment. Activation of mania/hypomania has also been reported in a small proportion of patients with major affective disorders treated with racemic citalopram and other marketed drugs effective in the treatment of major depressive disorder. Prior to initiating treatment with Lexapro, screen patients for any personal or family history of bipolar disorder, mania, or hypomania [see Dosage and Administration (2.4)].

5.6 Hyponatremia

Hyponatremia may occur as a result of treatment with SSRIs, including Lexapro. In many cases, this hyponatremia appears to be the result of the syndrome of inappropriate antidiuretic hormone secretion (SIADH), and was reversible when Lexapro was discontinued. Cases with serum sodium lower than 110 mmol/L have been reported. Elderly patients may be at greater risk of developing hyponatremia with SSRIs and SNRIs. Also, patients taking diuretics or who are otherwise volume depleted may be at greater risk [see Use in Specific Populations (8.5)]. Consider discontinuation of Lexapro in patients with symptomatic hyponatremia and appropriate medical intervention should be instituted.

Signs and symptoms of hyponatremia include headache, difficulty concentrating, memory impairment, confusion, weakness, and unsteadiness, which may lead to falls. Signs and symptoms associated with more severe and/or acute cases have included hallucination, syncope, seizure, coma, respiratory arrest, and death.

5.7 Increased Risk of Bleeding

Drugs that interfere with serotonin reuptake inhibition, including Lexapro, increase the risk of bleeding events. Concomitant use of aspirin, nonsteroidal anti-inflammatory drugs (NSAIDs), other antiplatelet drugs, warfarin, and other anticoagulants may add to the risk. Case reports and epidemiological studies (case-control and cohort design) have demonstrated an association between use of drugs that interfere with serotonin reuptake and the occurrence of gastrointestinal bleeding. Based on data from the published observational studies, exposure to SSRIs, particularly in the month before delivery, has been associated with a less than 2-fold increase in the risk of postpartum hemorrhage [see Use in Specific Populations (8.1)]. Bleeding events related to drugs that interfere with serotonin reuptake have ranged from ecchymoses, hematomas, epistaxis, and petechiae to life-threatening hemorrhages.

Inform patients about the increased risk of bleeding associated with the concomitant use of Lexapro and antiplatelet agents or anticoagulants. For patients taking warfarin, carefully monitor the international normalized ratio [see Drug Interactions (7)].

5.8 Interference with Cognitive and Motor Performance

In a study in normal volunteers, Lexapro 10 mg daily did not produce impairment of intellectual function or psychomotor performance. Because any psychoactive drug may impair judgment, thinking, or motor skills, however, patients should be cautioned about operating hazardous machinery, including automobiles, until they are reasonably certain that Lexapro therapy does not affect their ability to engage in such activities.

5.9 Angle Closure Glaucoma

The pupillary dilation that occurs following use of many antidepressant drugs, including Lexapro, may trigger an angle closure attack in a patient with anatomically narrow angles who does not have a patent iridectomy.

5.10 Use in Patients with Concomitant Illness

Clinical experience with Lexapro in patients with certain concomitant systemic illnesses is limited. Caution is advisable in using Lexapro in patients with diseases or conditions that produce altered metabolism or hemodynamic responses.

Lexapro has not been systematically evaluated in patients with a recent history of myocardial infarction or unstable heart disease. Patients with these diagnoses were generally excluded from clinical studies during the product's premarketing testing.

In subjects with hepatic impairment, clearance of racemic citalopram was decreased and plasma concentrations were increased. The recommended dose of Lexapro in hepatically impaired patients is 10 mg daily [see Dosage and Administration (2.5) and Use in Specific Populations (8.6)].

Because escitalopram is extensively metabolized, excretion of unchanged drug in urine is a minor route of elimination. Until adequate numbers of patients with severe renal impairment have been evaluated during chronic treatment with Lexapro, however, it should be used with caution in such patients [see Dosage and Administration (2.5) and Use in Specific Populations (8.7)].

5.11 Sexual Dysfunction

Use of SSRIs, including Lexapro, may cause symptoms of sexual dysfunction [see Adverse Reactions (6.1)]. In male patients, SSRI use may result in ejaculatory delay or failure, decreased libido, and erectile dysfunction. In female patients, SSRI use may result in decreased libido and delayed or absent orgasm.

It is important for prescribers to inquire about sexual function prior to initiation of Lexapro and to inquire specifically about changes in sexual function during treatment, because sexual function may not be spontaneously reported. When evaluating changes in sexual function, obtaining a detailed history (including timing of symptom onset) is important because sexual symptoms may have other causes, including the underlying psychiatric disorder. Discuss potential management strategies to support patients in making informed decisions about treatment.

6 ADVERSE REACTIONS

The following adverse reactions are discussed in greater detail in other sections of the labeling:

- Suicidal thoughts and behaviors in adolescents and young adults [see Warnings and Precautions (5.1)]
- Serotonin syndrome [see Warnings and Precautions (5.2)]
- Discontinuation syndrome [see Warnings and Precautions (5.3)]
- Seizures [see Warnings and Precautions (5.4)]
- Activation of mania or hypomania [see Warnings and Precautions (5.5)]
- Hyponatremia [see Warnings and Precautions (5.6)]
- Increased Risk of Bleeding [see Warnings and Precautions (5.7)]
- Interference with Cognitive and Motor Performance [see Warnings and Precautions (5.8)]
- Angle-closure glaucoma [see Warnings and Precautions (5.9)]
- Use in Patients with Concomitant Illness [see Warnings and Precautions (5.10)]
- Sexual Dysfunction [see Warnings and Precautions (5.11)]

6.1 Clinical Trials Experience

Because clinical studies are conducted under widely varying conditions, adverse reaction rates observed in the clinical studies of a drug cannot be directly compared to rates in the clinical studies of another drug and may not reflect the rates observed in practice.

Clinical Trial Data Sources

Adults
Adverse reactions information for Lexapro was collected from 715 patients with major depressive disorder who were exposed to escitalopram and from 592 patients who were exposed to placebo in double-blind, placebo-controlled trials. An additional 284 patients with major depressive disorder were newly exposed to escitalopram in open-label trials. The adverse reaction information for Lexapro in patients with GAD was collected from 429 patients exposed to escitalopram and from 427 patients exposed to placebo in double-blind, placebo-controlled trials.

Adverse reactions during exposure were obtained primarily by general inquiry and recorded by clinical investigators using terminology of their own choosing. Consequently, it is not possible to provide a meaningful estimate of the proportion of individuals experiencing adverse reactions without first grouping similar types of reactions into a smaller number of standardized event categories. In the tables and tabulations that follow, standard World Health Organization (WHO) terminology has been used to classify reported adverse reactions.

The stated frequencies of adverse reactions represent the proportion of individuals who experienced, at least once, a treatment emergent adverse event of the type listed. An event was considered treatment-emergent if it occurred for the first time or worsened while receiving therapy following baseline evaluation.

Pediatric Patients

Adverse reaction information for pediatric patients was collected in double-blind placebo-controlled studies in 576 pediatric patients 6 to 17 years of age, (286 Lexapro, 290 placebo) with major depressive disorder and in 273 pediatric patients 7 to 17 years of age (137 Lexapro, 136 placebo) with generalized anxiety disorder.

The safety and effectiveness of Lexapro have not been established in pediatric patients less than 12 years of age with MDD or less than 7 years of age with GAD.

Adverse Reactions Associated with Discontinuation of Treatment

Major Depressive Disorder

Adults
Among the 715 depressed patients who received Lexapro in placebo-controlled trials, 6% discontinued treatment due to an adverse event, as compared to 2% of 592 patients receiving placebo. In two fixed-dose studies, the rate of discontinuation for adverse reactions in patients receiving 10 mg/day Lexapro was not significantly different from the rate of discontinuation for adverse reactions in patients receiving placebo. The rate of discontinuation for adverse reactions in patients assigned to a fixed dose of 20 mg/day Lexapro was 10%, which was significantly different from the rate of discontinuation for adverse reactions in patients receiving 10 mg/day Lexapro (4%) and placebo (3%). Adverse reactions that were associated with the discontinuation of at least 1% of patients treated with Lexapro, and for which the rate was at least twice that of placebo, were nausea (2%) and ejaculation disorder (2% of male patients).

Pediatric Patients

Adverse reactions in pediatric patients 6 to 17 years of age were associated with discontinuation of 3.5% of 286 patients receiving Lexapro and 1% of 290 patients receiving placebo. The most common adverse reaction (incidence at least 1% for Lexapro and greater than placebo) associated with discontinuation was insomnia (1% Lexapro, 0% placebo).

The safety and effectiveness of Lexapro have not been established in pediatric patients less than 12 years of age with MDD.

Generalized Anxiety Disorder

Adults
Among the 429 GAD patients who received Lexapro 10 to 20 mg/day in placebo-controlled trials, 8% discontinued treatment due to an adverse event, as compared to 4% of 427 patients receiving placebo. Adverse reactions that were associated with the discontinuation of at least 1% of patients treated with Lexapro, and for which the rate was at least twice the placebo rate, were nausea (2%), insomnia (1%), and fatigue (1%).

Pediatric Patients

Adverse reactions in pediatric patients 7 to 17 years were associated with discontinuation of 2.9% of 137 patients receiving Lexapro and 1.5% of 136 patients receiving placebo. The most common adverse reaction (incidence at least 1% for Lexapro and greater than placebo) associated with discontinuation was activation syndrome (1% Lexapro, 0% placebo), intentional self injury (1% Lexapro, 0% placebo), epistaxis (1% Lexapro, 0% placebo), and nausea (1% Lexapro, 0% placebo).

Incidence of Adverse Reactions in Placebo-Controlled Clinical Trials

Major Depressive Disorder

Adults

The most commonly observed adverse reactions in Lexapro patients (incidence of approximately 5% or greater and approximately twice the incidence in placebo patients) were insomnia, ejaculation disorder (primarily ejaculatory delay), nausea, sweating increased, fatigue, and somnolence.

Table 2 enumerates the incidence, rounded to the nearest percent, of adverse reactions that occurred among 715 depressed patients who received Lexapro at doses ranging from 10 to 20 mg/day in placebo-controlled trials. Reactions included are those occurring in 2% or more of patients treated with Lexapro and for which the incidence in patients treated with Lexapro was greater than the incidence in placebo-treated patients.

TABLE 2
Adverse Reactions observed with a frequency of ≥ 2% and greater than placebo for Major Depressive Disorder (Adults)
Adverse Reaction | Lexapro | Placebo
 | (N=715) % | (N=592) %
Autonomic Nervous System Disorders
Dry Mouth | 6% | 5%
Sweating Increased | 5% | 2%
Central & Peripheral Nervous System Disorders
Dizziness | 5% | 3%
Gastrointestinal Disorders
Nausea | 15% | 7%
Diarrhea | 8% | 5%
Constipation | 3% | 1%
Indigestion | 3% | 1%
Abdominal Pain | 2% | 1%
General
Influenza-like Symptoms | 5% | 4%
Fatigue | 5% | 2%
Psychiatric Disorders
Insomnia | 9% | 4%
Somnolence | 6% | 2%
Appetite Decreased | 3% | 1%
Libido Decreased | 3% | 1%
Respiratory System Disorders
Rhinitis | 5% | 4%
Sinusitis | 3% | 2%
Urogenital
Ejaculation Disorder^1,2 | 9% | <1%
Impotence^2 | 3% | <1%
Anorgasmia^3 | 2% | <1%
^1Primarily ejaculatory delay.
^2Denominator used was for males only (N=225 Lexapro; N=188 placebo).
^3Denominator used was for females only (N=490 Lexapro; N=404 placebo).

Pediatric Patients

The overall profile of adverse reactions in pediatric patients 6 to 17 years in major depressive disorder was generally similar to that seen in adult studies, as shown in Table 2. However, the following adverse reactions (excluding those which appear in Table 2 and those for which the coded terms were uninformative or misleading) were reported at an incidence of at least 2% for Lexapro and greater than placebo: back pain, urinary tract infection, vomiting, and nasal congestion.

The safety and effectiveness of Lexapro have not been established in pediatric patients less than 12 years of age with MDD.

Generalized Anxiety Disorder

Adults

The most commonly observed adverse reactions in Lexapro patients (incidence of approximately 5% or greater and approximately twice the incidence in placebo patients) were nausea, ejaculation disorder (primarily ejaculatory delay), insomnia, fatigue, decreased libido, and anorgasmia.

Table 3 enumerates the incidence, rounded to the nearest percent of treatment-emergent adverse reactions that occurred among 429 GAD patients who received Lexapro 10 to 20 mg/day in placebo-controlled trials. Reactions included are those occurring in 2% or more of patients treated with Lexapro and for which the incidence in patients treated with Lexapro was greater than the incidence in placebo-treated patients.

TABLE 3
Adverse Reactions Observed with a Frequency of ≥ 2% and > placebo for Generalized Anxiety Disorder (Adults)
Adverse Reactions | Lexapro | Placebo
 | (N=429) % | (N=427) %
Autonomic Nervous System Disorders
Dry Mouth | 9% | 5%
Sweating Increased | 4% | 1%
Central & Peripheral Nervous System Disorders
Headache | 24% | 17%
Paresthesia | 2% | 1%
Gastrointestinal Disorders
Nausea | 18% | 8%
Diarrhea | 8% | 6%
Constipation | 5% | 4%
Indigestion | 3% | 2%
Vomiting | 3% | 1%
Abdominal Pain | 2% | 1%
Flatulence | 2% | 1%
Toothache | 2% | 0%
General
Fatigue | 8% | 2%
Influenza-like Symptoms | 5% | 4%
Musculoskeletal System Disorder
Neck/Shoulder Pain | 3% | 1%
Psychiatric Disorders
Somnolence | 13% | 7%
Insomnia | 12% | 6%
Libido Decreased | 7% | 2%
Dreaming Abnormal | 3% | 2%
Appetite Decreased | 3% | 1%
Lethargy | 3% | 1%
Respiratory System Disorders
Yawning | 2% | 1%
Urogenital
Ejaculation Disorder^1,2 | 14% | 2%
Anorgasmia^3 | 6% | <1%
Menstrual Disorder | 2% | 1%
^1Primarily ejaculatory delay.
^2Denominator used was for males only (N=182 Lexapro; N=195 placebo).
^3Denominator used was for females only (N=247 Lexapro; N=232 placebo).

Pediatric Patients

The overall profile of adverse reactions in pediatric patients 7 to 17 years in generalized anxiety disorder was generally similar to that seen in adult studies, as shown in Table 3. However, the following adverse reactions (excluding those which appear in Table 3) were reported at an incidence of at least 2% for Lexapro and greater than placebo: dizziness (3% Lexapro and 2% placebo), nasopharyngitis (3% Lexapro and 1% placebo), abdominal discomfort (3% Lexapro and 1% placebo), anxiety (3% Lexapro and 1% placebo), irritability (2% Lexapro and 1% placebo), and anger (2% Lexapro and 0% placebo).

Dose Dependency of Adverse Reactions
The potential dose dependency of common adverse reactions (defined as an incidence rate of ≥5% in either the 10 mg or 20 mg Lexapro groups) was examined on the basis of the combined incidence of adverse reactions in two fixed-dose trials. The overall incidence rates of adverse reactions in 10 mg Lexapro-treated patients (66%) was similar to that of the placebo-treated patients (61%), while the incidence rate in 20 mg/day Lexapro-treated patients was greater (86%). Table 4 shows common adverse reactions that occurred in the 20 mg/day Lexapro group with an incidence that was approximately twice that of the 10 mg/day Lexapro group and approximately twice that of the placebo group.

TABLE 4
Incidence of Common Adverse Reactions in Patients with Major
Depressive Disorder
Adverse Reaction | Placebo | 10 mg/day | 20 mg/day
 | (N=311) | Lexapro | Lexapro
 |  | (N=310) | (N=125)
Insomnia | 4% | 7% | 14%
Diarrhea | 5% | 6% | 14%
Dry Mouth | 3% | 4% | 9%
Somnolence | 1% | 4% | 9%
Dizziness | 2% | 4% | 7%
Sweating Increased | <1% | 3% | 8%
Constipation | 1% | 3% | 6%
Fatigue | 2% | 2% | 6%
Indigestion | 1% | 2% | 6%

Male and Female Sexual Dysfunction with SSRIs
Although changes in sexual desire, sexual performance, and sexual satisfaction often occur as manifestations of a psychiatric disorder, they may also be a consequence of pharmacologic treatment. In particular, some evidence suggests that SSRIs can cause such untoward sexual experiences.

Reliable estimates of the incidence and severity of untoward experiences involving sexual desire, performance, and satisfaction are difficult to obtain, however, in part because patients and physicians may be reluctant to discuss them. Accordingly, estimates of the incidence of untoward sexual experience and performance cited in product labeling are likely to underestimate their actual incidence.

TABLE 5
Incidence of Sexual Side Effects in Placebo-Controlled Clinical Trials
Adverse Event | Lexapro | Placebo
 | In Males Only
 | (N=407) | (N=383)
Ejaculation Disorder (primarily ejaculatory delay) | 12% | 1%
Libido Decreased | 6% | 2%
Impotence | 2% | <1%
 | In Females Only
 | (N=737) | (N=636)
Libido Decreased | 3% | 1%
Anorgasmia | 3% | <1%

There are no adequately designed studies examining sexual dysfunction with escitalopram treatment.

Priapism has been reported with all SSRIs.

While it is difficult to know the precise risk of sexual dysfunction associated with the use of SSRIs, physicians should routinely inquire about such possible side effects.

Vital Sign Changes

Lexapro and placebo groups were compared with respect to (1) mean change from baseline in vital signs (pulse, systolic blood pressure, and diastolic blood pressure) and (2) the incidence of patients meeting criteria for potentially clinically significant changes from baseline in these variables. These analyses did not reveal any clinically important changes in vital signs associated with Lexapro treatment. In addition, a comparison of supine and standing vital sign measures in subjects receiving Lexapro indicated that Lexapro treatment is not associated with orthostatic changes.

Weight Changes

Patients treated with Lexapro in controlled trials did not differ from placebo-treated patients with regard to clinically important change in body weight.

Laboratory Changes

Lexapro and placebo groups were compared with respect to (1) mean change from baseline in various serum chemistry, hematology, and urinalysis variables, and (2) the incidence of patients meeting criteria for potentially clinically significant changes from baseline in these variables. These analyses revealed no clinically important changes in laboratory test parameters associated with Lexapro treatment.

ECG Changes

Electrocardiograms from Lexapro (N=625) and placebo (N=527) groups were compared with respect to outliers defined as subjects with QTc changes over 60 msec from baseline or absolute values over 500 msec post-dose, and subjects with heart rate increases to over 100 bpm or decreases to less than 50 bpm with a 25% change from baseline (tachycardic or bradycardic outliers, respectively). None of the patients in the Lexapro group had a QTcF interval >500 msec or a prolongation >60 msec compared to 0.2% of patients in the placebo group. The incidence of tachycardic outliers was 0.2% in the Lexapro and the placebo group. The incidence of bradycardic outliers was 0.5% in the Lexapro group and 0.2% in the placebo group.

QTcF interval was evaluated in a randomized, placebo and active (moxifloxacin 400 mg) controlled cross-over, escalating multiple dose study in 113 healthy subjects. The maximum mean (95% upper confidence bound) difference from placebo arm were 4.5 (6.4) and 10.7 (12.7) msec for 10 mg and supratherapeutic 30 mg escitalopram given once daily, respectively. Based on the established exposure-response relationship, the predicted QTcF change from placebo arm (95% confidence interval) under the Cmax for the dose of 20 mg is 6.6 (7.9) msec. Escitalopram 30 mg given once daily resulted in mean Cmax of 1.7-fold higher than the mean Cmax for the maximum recommended therapeutic dose at steady state (20 mg). The exposure under supratherapeutic 30 mg dose is similar to the steady state concentrations expected in CYP2C19 poor metabolizers following a therapeutic dose of 20 mg.

Other Reactions Observed During the Premarketing Evaluation of Lexapro

Following is a list of treatment-emergent adverse reactions, as defined in the introduction to the ADVERSE REACTIONS section, reported by the 1428 patients treated with Lexapro for periods of up to one year in double-blind or open-label clinical trials during its premarketing evaluation. The listing does not include those reactions already listed in Tables 2 & 3, those reactions for which a drug cause was remote and at a rate less than 1% or lower than placebo, those reactions which were so general as to be uninformative, and those reactions reported only once which did not have a substantial probability of being acutely life threatening. Reactions are categorized by body system. Reactions of major clinical importance are described in the Warnings and Precautions section (5).

Cardiovascular: hypertension, palpitation.

Central and Peripheral Nervous System Disorders: light-headed feeling, migraine.

Gastrointestinal Disorders: abdominal cramp, heartburn, gastroenteritis.

General: allergy, chest pain, fever, hot flushes, pain in limb.

Metabolic and Nutritional Disorders: increased weight.

Musculoskeletal System Disorders: arthralgia, myalgia jaw stiffness.

Psychiatric Disorders: appetite increased, concentration impaired, irritability.

Reproductive Disorders/Female: menstrual cramps, menstrual disorder.

Respiratory System Disorders: bronchitis, coughing, nasal congestion, sinus congestion, sinus headache.

Skin and Appendages Disorders: rash.

Special Senses: vision blurred, tinnitus.

Urinary System Disorders: urinary frequency, urinary tract infection.

6.2 Post-Marketing Experience

Adverse Reactions Reported Subsequent to the Marketing of Escitalopram

The following adverse reactions have been identified during post-approval use of Lexapro. Because these reactions are reported voluntarily from a population of uncertain size, it is not always possible to reliably estimate their frequency or establish a causal relationship to drug exposure.

Blood and Lymphatic System Disorders: anemia, agranulocytis, aplastic anemia, hemolytic anemia, idiopathic thrombocytopenia purpura, leukopenia, thrombocytopenia.

Cardiac Disorders: atrial fibrillation, bradycardia, cardiac failure, myocardial infarction, tachycardia, torsade de pointes, ventricular arrhythmia, ventricular tachycardia.

Ear and labyrinth disorders: vertigo

Endocrine Disorders: diabetes mellitus, hyperprolactinemia, SIADH.

Eye Disorders: angle closure glaucoma, diplopia, mydriasis, visual disturbance.

Gastrointestinal Disorder: dysphagia, gastrointestinal hemorrhage, gastroesophageal reflux, pancreatitis, rectal hemorrhage.

General Disorders and Administration Site Conditions: abnormal gait, asthenia, edema, fall, feeling abnormal, malaise.

Hepatobiliary Disorders: fulminant hepatitis, hepatic failure, hepatic necrosis, hepatitis.

Immune System Disorders: allergic reaction, anaphylaxis.

Investigations: bilirubin increased, decreased weight, electrocardiogram QT prolongation, hepatic enzymes increased, hypercholesterolemia, INR increased, prothrombin decreased.

Metabolism and Nutrition Disorders: hyperglycemia, hypoglycemia, hypokalemia, hyponatremia.

Musculoskeletal and Connective Tissue Disorders: muscle cramp, muscle stiffness, muscle weakness, rhabdomyolysis.

Nervous System Disorders: akathisia, amnesia, ataxia, choreoathetosis, cerebrovascular accident, dysarthria, dyskinesia, dystonia, extrapyramidal disorders, grand mal seizures (or convulsions), hypoaesthesia, myoclonus, nystagmus, Parkinsonism, restless legs, seizures, syncope, tardive dyskinesia, tremor.

Pregnancy, Puerperium and Perinatal Conditions: spontaneous abortion.

Psychiatric Disorders: acute psychosis, aggression, agitation, anger, anxiety, apathy, completed suicide, confusion, depersonalization, depression aggravated, delirium, delusion, disorientation, feeling unreal, hallucinations (visual and auditory), mood swings, nervousness, nightmare, panic reaction, paranoia, restlessness, self-harm or thoughts of self-harm, suicide attempt, suicidal ideation, suicidal tendency.

Renal and Urinary Disorders: acute renal failure, dysuria, urinary retention.

Reproductive System and Breast Disorders: menorrhagia, priapism.

Respiratory, Thoracic and Mediastinal Disorders: anosmia, dyspnea, epistaxis, pulmonary embolism, hyposmia, pulmonary hypertension of the newborn.

Skin and Subcutaneous Tissue Disorders: alopecia, angioedema, dermatitis, drug reaction with eosinophilia and systemic symptoms (DRESS), ecchymosis, erythema multiforme, photosensitivity reaction, Stevens Johnson Syndrome, toxic epidermal necrolysis, urticaria.

Vascular Disorders: deep vein thrombosis, flushing, hypertensive crisis, hypotension, orthostatic hypotension, phlebitis, thrombosis.

7 DRUG INTERACTIONS

Table 6 presents clinically important drug interactions with Lexapro.

TABLE 6 Clinically Important Drug Interactions with Lexapro
Monoamine Oxidase Inhibitors (MAOIs)
Clinical Impact: | Concomitant use of SSRIs, including Lexapro, and MAOIs increases the risk of serotonin syndrome.
Intervention: | Lexapro is contraindicated in patients taking MAOIs, including MAOIs such as linezolid or intravenous methylene blue [see Dosage and Administration (2.7), Contraindications (4), and Warnings and Precautions (5.2)].
Pimozide
Clinical Impact: | Concomitant use of racemic citalopram with pimozide increases plasma concentrations of pimozide, a drug with a narrow therapeutic index, and may increase the risk of QT prolongation and/or ventricular arrhythmias compared to use of racemic citalopram alone [see Clinical Pharmacology (12.3)].
Intervention: | Lexapro is contraindicated in patients taking pimozide [see Contraindications (4)].
Other Serotonergic Drugs
Clinical Impact: | Concomitant use of Lexapro and other serotonergic drugs (including other SSRIs, SNRIs, triptans, tricyclic antidepressants, opioids, lithium, buspirone, amphetamines, tryptophan, and St. John's Wort) increases the risk of serotonin syndrome.
Intervention: | Monitor patients for signs and symptoms of serotonin syndrome, particularly during Lexapro initiation and dosage increases. If serotonin syndrome occurs, consider discontinuation of Lexapro and/or concomitant serotonergic drugs [see Warning and Precautions (5.2)].
Drugs That Interfere With Hemostasis (NSAIDs, Aspirin, Warfarin, etc.)
Clinical Impact: | Concomitant use of Lexapro and an antiplatelet or anticoagulant may potentiate the risk of bleeding.
Intervention: | Inform patients of the increased risk of bleeding associated with the concomitant use of Lexapro and antiplatelet agents and anticoagulants. For patients taking warfarin, carefully monitor the international normalized ratio [see Warning and Precautions (5.7)].
Sumatriptan
Clinical Impact: | There have been postmarketing reports describing patients with weakness, hyperreflexia, and incoordination following the use of an SSRI and sumatriptan.
Intervention: | If concomitant treatment with sumatriptan and an SSRI is clinically warranted, appropriate observation of the patient is advised [see Warning and Precautions (5.2)].
Carbamazepine
Clinical Impact: | Combined administration of racemic citalopram (40 mg/day for 14 days) and carbamazepine (titrated to 400 mg/day for 35 days) did not significantly affect the pharmacokinetics of carbamazepine, a CYP3A4 substrate.
Intervention: | Although trough citalopram plasma levels were unaffected, given the enzyme-inducing properties of carbamazepine, the possibility that carbamazepine might increase the clearance of escitalopram should be considered if the two drugs are coadministered.
Drugs Metabolized by CYP2D6
Clinical Impact: | Coadministration of escitalopram (20 mg/day for 21 days) with the tricyclic antidepressant desipramine (single dose of 50 mg), a substrate for CYP2D6, resulted in a 40% increase in Cmax and a 100% increase in AUC of desipramine.
Intervention: | The clinical significance of this finding is unknown. Exercise caution during coadministration of escitalopram and drugs metabolized by CYP2D6.

8 USE IN SPECIFIC POPULATIONS

8.1 Pregnancy

Pregnancy Exposure Registry

There is a pregnancy exposure registry that monitors pregnancy outcomes in women exposed to antidepressants during pregnancy. Healthcare providers are encouraged to advise patients to register by calling the National Pregnancy Registry for Antidepressants at 1-844-405-6185 or visiting online at https://womensmentalhealth.org/research/pregnancyregistry/antidepressants.

Risk Summary

Based on data from published observational studies, exposure to SSRIs, particularly in the month before delivery, has been associated with a less than 2-fold increase in the risk of postpartum hemorrhage [see Warnings and Precautions (5.7) and Clinical Considerations].

Available data from published epidemiologic studies and postmarketing reports have not established an increased risk of major birth defects or miscarriage. There are risks of persistent pulmonary hypertension of the newborn (PPHN) (see Data) and poor neonatal adaptation (see Clinical Considerations) with exposure to selective serotonin reuptake inhibitors (SSRIs), including LEXAPRO, during pregnancy. There are risks associated with untreated depression in pregnancy (see Clinical Considerations).

In animal reproduction studies, both escitalopram and racemic citalopram have been shown to have adverse effects on embryo/fetal and postnatal development, including fetal structural abnormalities, when administered at doses greater than human therapeutic doses (see Data).

The estimated background risk of major birth defects and miscarriage for the indicated population is unknown. All pregnancies have a background risk of birth defect, loss, or other adverse outcomes. In the U.S. general population, the estimated background risk of major birth defects and miscarriage in the clinically recognized pregnancies is 2 to 4% and 15 to 20%, respectively.

Clinical Considerations

Disease-associated maternal risk and/or embryo/fetal risk

Women who discontinue antidepressants are more likely to experience a relapse of major depression than women who continue antidepressants. This finding is from a prospective longitudinal study of 201 pregnant women with a history of major depression, who were euthymic and taking antidepressants at the beginning of pregnancy. Consider the risk of untreated depression when discontinuing or changing treatment with antidepressant medication during pregnancy and postpartum.

Maternal Adverse Reactions

Use of Lexapro in the month before delivery may be associated with an increased risk of postpartum hemorrhage [see Warnings and Precautions (5.7)].

Fetal/Neonatal adverse reactions

Neonates exposed to SSRIs or SNRIs, including Lexapro, late in third trimester have developed complications requiring prolonged hospitalization, respiratory support, and tube feeding. Such complications can arise immediately upon delivery. Reported clinical findings have included respiratory distress, cyanosis, apnea, seizures, temperature instability, feeding difficulty, vomiting, hypoglycemia, hypotonia, hypertonia, hyperreflexia, tremor, jitteriness, irritability, and constant crying. These features are consistent with either a direct toxic effect of SSRIs and SNRIs or, possibly, a drug discontinuation syndrome. It should be noted that, in some cases, the clinical picture is consistent with serotonin syndrome [see Warnings and Precautions (5.2)].

Data

Human Data

Exposure to SSRIs, particularly later in pregnancy, may increase the risk for PPHN. PPHN occurs in 1-2 per 1000 live births in the general populations and is associated with substantial neonatal morbidity and mortality.

Animal Data

In a rat embryo/fetal development study, oral administration of escitalopram (56, 112, or 150 mg/kg/day) to pregnant animals during the period of organogenesis resulted in decreased fetal body weight and associated delays in ossification at the two higher doses [approximately ≥ 55 times the maximum recommended human dose (MRHD) of 20 mg/day on a mg/m^2 basis]. Maternal toxicity (clinical signs and decreased body weight gain and food consumption), mild at 56 mg/kg/day, was present at all dose levels. The developmental no-effect dose of 56 mg/kg/day is approximately 27 times the MRHD of 20 mg on a mg/m^2 basis. No malformations were observed at any of the doses tested (as high as 73 times the MRHD on a mg/m^2 basis).

When female rats were treated with escitalopram (6, 12, 24, or 48 mg/kg/day) during pregnancy and through weaning, slightly increased offspring mortality and growth retardation were noted at 48 mg/kg/day which is approximately 23 times the MRHD of 20 mg on a mg/m^2 basis. Slight maternal toxicity (clinical signs and decreased body weight gain and food consumption) was seen at this dose. Slightly increased offspring mortality was also seen at 24 mg/kg/day. The no-effect dose was 12 mg/kg/day which is approximately 6 times the MRHD of 20 mg on a mg/m^2 basis.

In two rat embryo/fetal development studies, oral administration of racemic citalopram (32, 56, or 112 mg/kg/day) to pregnant animals during the period of organogenesis resulted in decreased embryo/fetal growth and survival and an increased incidence of fetal abnormalities (including cardiovascular and skeletal defects) at the high dose, which is approximately 18 times the MRHD of 60 mg/day on a mg/m^2 basis. This dose was also associated with maternal toxicity (clinical signs, decreased body weight gain). The developmental no-effect dose was 56 mg/kg/day is approximately 9 times the MRHD on a mg/m^2 basis. In a rabbit study, no adverse effects on embryo/fetal development were observed at doses of racemic citalopram of up to 16 mg/kg/day, or approximately 5 times the MRHD on a mg/m^2 basis. Thus, developmental effects of racemic citalopram were observed at a maternally toxic dose in the rat and were not observed in the rabbit.

When female rats were treated with racemic citalopram (4.8, 12.8, or 32 mg/kg/day) from late gestation through weaning, increased offspring mortality during the first 4 days after birth and persistent offspring growth retardation were observed at the highest dose, which is approximately 5 times the MRHD of 60 mg on a mg/m^2 basis. The no-effect dose was 12.8 mg/kg/day is approximately 2 times the MRHD on a mg/m^2 basis. Similar effects on offspring mortality and growth were seen when dams were treated throughout gestation and early lactation at doses ≥ 24 mg/kg/day, approximately 4 times the MRHD on a mg/m^2 basis. A no-effect dose was not determined in that study.

8.2 Lactation

Risk Summary

Data from the published literature report the presence of escitalopram and desmethylescitalopram in human milk (see Data). There are reports of excessive sedation, restlessness, agitation, poor feeding and poor weight gain in infants exposed to escitalopram, through breast milk (see Clinical Considerations). There are no data on the effects of escitalopram or its metabolites on milk production. The developmental and health benefits of breastfeeding should be considered along with the mother’s clinical need for LEXAPRO and any potential adverse effects on the breastfed child from LEXAPRO or from the underlying maternal condition.

Clinical Considerations

Infants exposed to LEXAPRO should be monitored for excess sedation, restlessness, agitation, poor feeding and poor weight gain.

Data

A study of 8 nursing mothers on escitalopram with daily doses of 10-20 mg/day showed that exclusively breast-fed infants receive approximately 3.9% of the maternal weight-adjusted dose of escitalopram and 1.7% of the maternal weight-adjusted dose of desmethylcitalopram.

8.4 Pediatric Use

Major Depressive Disorder

The safety and effectiveness of Lexapro for the treatment of major depressive disorder have been established in pediatric patients 12 years of age and older. Use of Lexapro for this indication is supported by evidence from adequate and well-controlled studies in adults with additional evidence from an 8-week, flexible-dose, placebo-controlled study that compared Lexapro 10 mg to 20 mg once daily to placebo in pediatric patients 12 to 17 years of age with major depressive disorder [see Clinical Studies (14.1)]. The safety of Lexapro was similar to adult patients with MDD [see Adverse Reactions (6.1)].

The safety and effectiveness of Lexapro for the treatment of major depressive disorder have not been established in pediatric patients younger than 12 years of age. In a 24-week, open- label safety study in 118 pediatric patients aged 7 to 11 years who had major depressive disorder, the safety findings were consistent with the known safety and tolerability profile for Lexapro.

Generalized Anxiety Disorder

The safety and effectiveness of Lexapro for the treatment of generalized anxiety disorder have been established in pediatric patients 7 years of age and older. Use of Lexapro for this indication is supported by evidence from adequate and well-controlled studies in adults with additional evidence from an 8-week, flexible-dose, placebo-controlled study that compared Lexapro 10 mg to 20 mg once daily to placebo in pediatric patients 7 to 17 years of age with GAD [see Clinical Studies (14.2)]. The safety of Lexapro was similar to adult patients with GAD [see Adverse Reactions (6.1)].

The safety and effectiveness of Lexapro for the treatment of generalized anxiety disorder have not been established in pediatric patients younger than 7 years of age.

Antidepressants increase the risk of suicidal thoughts and behaviors in pediatric patients [see Warnings and Precautions (5.1)]. Decreased appetite and weight loss have been observed in association with the use of SSRIs. Consequently, regular monitoring of weight and growth should be performed in children and adolescents treated with an SSRI such as Lexapro.

Juvenile Animal Toxicity Data

In a juvenile animal study, male and female rats were administered escitalopram at 5, 40, or 80 mg/kg/day by oral gavage from postnatal day (PND) 21 to PND 69. A delay in sexual maturation was observed in both males and females at ≥ 40 mg/kg/day with a No Observed Adverse Effect Level (NOAEL) of 5 mg/kg/day. This NOAEL was associated with plasma AUC levels less than those measured at the maximum recommended dose (MRHD) in pediatrics (20 mg). However, there was no effect on reproductive function. Increased motor activity (both ambulatory and fine movements) was observed in females prior to daily dosing at ≥ 40 mg/kg/day (3.5 times the MRHD based on AUC levels). A reversible disruption of learning and memory function was observed in males at 80 mg/kg/day with a NOAEL of 40 mg/kg/day, which was associated with an AUC level 3.5 times those measured at the MRHD in pediatrics. There was no effect on learning and memory function in treated female rats.

8.5 Geriatric Use

Approximately 69 patients (6%) of the 1,144 patients receiving escitalopram in controlled trials of Lexapro in major depressive disorder and GAD were 60 years of age or older [see Clinical Studies (14.1, 14.2)]. The number of elderly patients in these trials was insufficient to adequately assess for possible differential efficacy and safety measures on the basis of age. Nevertheless, greater sensitivity of some elderly individuals to effects of Lexapro cannot be ruled out.

In two pharmacokinetic studies, escitalopram half-life was increased by approximately 50% in subjects 65 years and older as compared to young subjects and Cmax was unchanged [see Clinical Pharmacology (12.3)]. The recommended dosage of LEXAPRO for elderly patients is 10 mg daily [see Dosage and Administration (2.5)].

SSRIs, including Lexapro, have been associated with cases of clinically significant hyponatremia in elderly patients, who may be at greater risk for this adverse reaction [see Warnings and Precautions (5.6)].

Of 4,422 patients in clinical studies of racemic citalopram, 1,357 were 60 and over, 1,034 were 65 and over, and 457 were 75 and over. No overall differences in safety or effectiveness were observed between these subjects and younger subjects, and other reported clinical experience has not identified differences in responses between the geriatric and younger patients, but again, greater sensitivity of some elderly individuals cannot be ruled out.

8.6 Hepatic Impairment

Increased citalopram exposure occurs in patients with hepatic impairment [see Clinical Pharmacology (12.3)]. The recommended dosage of LEXAPRO in patients with hepatic impairment is 10 mg daily [see Dosage and Administration (2.5)].

8.7 Renal Impairment

Pharmacokinetics of Lexapro in patients with a creatinine clearance less than 20 mL/minute has not been evaluated. No dosage adjustment is necessary for patients with mild or moderate renal impairment [see Dosage and Administration (2.5), Clinical Pharmacology (12.3)].

9 DRUG ABUSE AND DEPENDENCE

9.2 Abuse and Dependence

Physical and Psychological Dependence

Animal studies suggest that the abuse liability of racemic citalopram is low. Lexapro has not been systematically studied in humans for its potential for abuse, tolerance, or physical dependence. The premarketing clinical experience with Lexapro did not reveal any drug-seeking behavior. However, these observations were not systematic and it is not possible to predict on the basis of this limited experience the extent to which a CNS-active drug will be misused, diverted, and/or abused once marketed. Consequently, physicians should carefully evaluate Lexapro patients for history of drug abuse and follow such patients closely, observing them for signs of misuse or abuse (e.g., development of tolerance, incrementations of dose, drug-seeking behavior).

10 OVERDOSAGE

The following have been reported with Lexapro tablet overdosage:

- Seizures, which may be delayed, and altered mental status including coma.
- Cardiovascular toxicity, which may be delayed, including QRS and QTc interval prolongation, wide complex tachyarrhythmias, and torsade de pointes. Hypertension most commonly seen, but rarely can see hypotension alone or with co-ingestants including alcohol.
- Serotonin syndrome (patients with a multiple drug overdosage with other proserotonergic drugs may have a higher risk).

Prolonged cardiac monitoring is recommended in Lexapro overdosage ingestions due to the arrhythmia risk.

Gastrointestinal decontamination with activated charcoal should be considered in patients who present early after a Lexapro overdose.

Consider contacting the Poison Help line (1-800-222-1222) or a medical toxicologist for additional overdose management recommendations.

11 DESCRIPTION

Lexapro contains escitalopram, a selective serotonin reuptake inhibitor (SSRI), present as escitalopram oxalate salt. Escitalopram is the pure S- enantiomer (single isomer) of the racemic bicyclic phthalane derivative citalopram. Escitalopram oxalate is designated S-(+)-1-[3(dimethyl-amino)propyl]-1-(p-fluorophenyl)-5-phthalancarbonitrile oxalate with the following structural formula:

The molecular formula is C20H21FN2O • C2H2O4 and the molecular weight is 414.40.

Escitalopram oxalate occurs as a fine, white to slightly-yellow powder and is freely soluble in methanol and dimethyl sulfoxide (DMSO), soluble in isotonic saline solution, sparingly soluble in water and ethanol, slightly soluble in ethyl acetate, and insoluble in heptane. Lexapro tablets, for oral use, are film-coated, round tablets containing 6.38 mg, 12.75 mg, 25.5 mg escitalopram oxalate in strengths equivalent to 5 mg, 10 mg, and 20 mg, respectively, of escitalopram base. The 10 and 20 mg tablets are scored. The tablets also contain the following inactive ingredients: talc, croscarmellose sodium, microcrystalline cellulose/colloidal silicon dioxide, and magnesium stearate. The film coating contains hypromellose, titanium dioxide, and polyethylene glycol.

Lexapro oral solution contains 1.29 mg/ml escitalopram oxalate equivalent to 1 mg/mL escitalopram base. It also contains the following inactive ingredients: sorbitol, purified water, citric acid, sodium citrate, malic acid, glycerin, propylene glycol, methylparaben, propylparaben, and natural peppermint flavor. The oral solution is not currently marketed.

12 CLINICAL PHARMACOLOGY

12.1 Mechanism of Action

The mechanism of antidepressant action of escitalopram, the S-enantiomer of racemic citalopram, is presumed to be linked to potentiation of serotonergic activity in the central nervous system (CNS) resulting from its inhibition of CNS neuronal reuptake of serotonin (5-HT).

12.2 Pharmacodynamics

In vitro and in vivo studies in animals suggest that escitalopram is a highly selective serotonin reuptake inhibitor (SSRI) with minimal effects on norepinephrine and dopamine neuronal reuptake. Escitalopram is at least 100-fold more potent than the R-enantiomer with respect to inhibition of 5-HT reuptake and inhibition of 5-HT neuronal firing rate. Tolerance to a model of antidepressant effect in rats was not induced by long-term (up to 5 weeks) treatment with escitalopram. Escitalopram has no or very low affinity for serotonergic (5-HT1-7) or other receptors including alpha- and beta-adrenergic, dopamine (D1-5), histamine (H1-3), muscarinic (M1-5), and benzodiazepine receptors. Escitalopram also does not bind to, or has low affinity for, various ion channels including Na^+, K^+, Cl^-, and Ca^++ channels. Antagonism of muscarinic, histaminergic, and adrenergic receptors has been hypothesized to be associated with various anticholinergic, sedative, and cardiovascular side effects of other psychotropic drugs.

12.3 Pharmacokinetics

The single- and multiple-dose pharmacokinetics of escitalopram are linear and dose-proportional in a dose range of 10 to 30 mg/day.

With once-daily dosing, steady state plasma concentrations are achieved within approximately one week. At steady state, the extent of accumulation of escitalopram in plasma in young healthy subjects was 2.2-2.5 times the plasma concentrations observed after a single dose.

Absorption

The absolute bioavailability of citalopram is about 80% relative to an intravenous dose. The tablet and the oral solution dosage forms of escitalopram oxalate are bioequivalent.

Following a single oral dose (20 mg tablet or solution) of escitalopram, peak blood levels occur at about 5 hours. Absorption of escitalopram is not affected by food.

Distribution

The binding of escitalopram to human plasma proteins is approximately 56%. The volume of distribution of citalopram is about 12 L/kg. Data specific on escitalopram are unavailable.

Elimination

Biotransformation of escitalopram is mainly hepatic, with a mean terminal half-life of about 27-32 hours. The oral clearance of escitalopram is 600 mL/min, with approximately 7% of that due to renal clearance.

Metabolism

Escitalopram is metabolized to S-DCT and S-didemethylcitalopram (S-DDCT). In humans, unchanged escitalopram is the predominant compound in plasma. At steady state, the concentration of the escitalopram metabolite S-DCT in plasma is approximately one-third that of escitalopram. The level of S-DDCT was not detectable in most subjects. In vitro studies show that escitalopram is at least 7 and 27 times more potent than S-DCT and S-DDCT, respectively, in the inhibition of serotonin reuptake, suggesting that the metabolites of escitalopram do not contribute significantly to the antidepressant actions of escitalopram. S-DCT and S-DDCT also have no or very low affinity for serotonergic (5-HT1-7) or other receptors including alpha- and beta-adrenergic, dopamine (D1-5), histamine (H1-3), muscarinic (M1-5), and benzodiazepine receptors. S-DCT and S-DDCT also do not bind to various ion channels including Na^+, K^+, Cl^-, and Ca^++ channels. In vitro studies using human liver microsomes indicated that CYP3A4 and CYP2C19 are the primary isozymes involved in the N-demethylation of escitalopram.

Excretion

Following oral administrations of escitalopram, the fraction of drug recovered in the urine as escitalopram and S-demethylcitalopram (S-DCT) is about 8% and 10%, respectively.

Specific Populations

Pediatric Patients

Pediatric patients 7 to 11 years of age: Based on population PK simulations, following multiple dosing of 20 mg/day escitalopram, steady-state Cmax and AUCtau of escitalopram were increased by 93% and 86%, respectively in pediatric patients with GAD 7 to 11 years of age compared to adults.

Pediatric patients 12 to 17 years of age: In a single dose study of 10 mg escitalopram, AUC of escitalopram decreased by 19%, and Cmax increased by 26% in healthy pediatric subjects 12 to 17 years of age compared to adults. Following multiple dosing of 40 mg/day citalopram, escitalopram elimination half-life, steady-state Cmax and AUC were similar in pediatric patients 12 to 17 years of age with MDD compared to adults [see Use in Specific Populations (8.4)].

Geriatric Patients

Escitalopram pharmacokinetics in subjects ≥ 65 years of age were compared to adults in a single-dose and a multiple-dose study. Escitalopram AUC and half-life were increased by approximately 50% in elderly subjects, and Cmax was unchanged [see Dosage and Administration (2.5), Use in Specific Populations (8.5)].

Male and Female Patients

Based on data from single- and multiple-dose studies measuring escitalopram in elderly, young adults, and adolescents, no dosage adjustment on the basis of gender is needed.

Patients with Hepatic Impairment

Citalopram oral clearance was reduced by 37% and half-life was doubled in patients with reduced hepatic function compared to normal subjects [see Dosage and Administration (2.5), Use in Specific Populations (8.6)].

Patients with Renal Impairment

In patients with mild to moderate renal function impairment, oral clearance of citalopram was reduced by 17% compared to normal subjects. No information is available about the pharmacokinetics of escitalopram in patients with severely reduced renal function (creatinine clearance < 20 mL/min) [see Use in Specific Populations (8.7)].

Drug Interaction Studies

In vitro enzyme inhibition data did not reveal an inhibitory effect of escitalopram on CYP3A4, -1A2, -2C9, -2C19, and -2E1. Based on in vitro data, escitalopram would be expected to have little inhibitory effect on in vivo metabolism mediated by these cytochromes. While in vivo data to address this question are limited, results from drug interaction studies suggest that escitalopram, at a dose of 20 mg, has no 3A4 inhibitory effect and a modest 2D6 inhibitory effect [see Drug Interactions (7)].

CYP3A4 and CYP2C19 Inhibitors

In vitro studies indicated that CYP3A4 and -2C19 are the primary enzymes involved in the metabolism of escitalopram. However, coadministration of escitalopram (20 mg) and ritonavir (600 mg), a potent inhibitor of CYP3A4, did not significantly affect the pharmacokinetics of escitalopram. Because escitalopram is metabolized by multiple enzyme systems, inhibition of a single enzyme may not appreciably decrease escitalopram clearance.

Cimetidine

In subjects who had received 21 days of 40 mg/day racemic citalopram, combined administration of 400 mg twice a day cimetidine for 8 days resulted in an increase in citalopram AUC and Cmax of 43% and 39%, respectively. The clinical significance of these findings is unknown.

Digoxin

In subjects who had received 21 days of 40 mg/day racemic citalopram, combined administration of citalopram and digoxin (single dose of 1 mg) did not significantly affect the pharmacokinetics of either citalopram or digoxin.

Lithium

Coadministration of racemic citalopram (40 mg/day for 10 days) and lithium (30 mmol/day for 5 days) had no significant effect on the pharmacokinetics of citalopram or lithium. Plasma lithium levels should be monitored with appropriate adjustment to the lithium dose in accordance with standard clinical practice. Because lithium may enhance the serotonergic effects of escitalopram, caution should be exercised when Lexapro and lithium are coadministered.

Theophylline

Combined administration of racemic citalopram (40 mg/day for 21 days) and the CYP1A2 substrate theophylline (single dose of 300 mg) did not affect the pharmacokinetics of theophylline. The effect of theophylline on the pharmacokinetics of citalopram was not evaluated.

Ketoconazole

Combined administration of racemic citalopram (40 mg) and ketoconazole (200 mg), a potent CYP3A4 inhibitor, decreased the Cmax and AUC of ketoconazole by 21% and 10%, respectively, and did not significantly affect the pharmacokinetics of citalopram.

Ritonavir

Combined administration of a single dose of ritonavir (600 mg), both a CYP3A4 substrate and a potent inhibitor of CYP3A4, and escitalopram (20 mg) did not affect the pharmacokinetics of either ritonavir or escitalopram.

Triazolam

Combined administration of racemic citalopram (titrated to 40 mg/day for 28 days) and the CYP3A4 substrate triazolam (single dose of 0.25 mg) did not significantly affect the pharmacokinetics of either citalopram or triazolam.

Metoprolol

Administration of 20 mg/day Lexapro for 21 days in healthy volunteers resulted in a 50% increase in Cmax and 82% increase in AUC of the beta-adrenergic blocker metoprolol (given in a single dose of 100 mg). Increased metoprolol plasma levels have been associated with decreased cardioselectivity. Coadministration of Lexapro and metoprolol had no clinically significant effects on blood pressure or heart rate.

Alcohol

Lexapro did not potentiate the cognitive and motor effects of alcohol in a clinical trial. As with other psychotropic medications, the use of alcohol by patients taking Lexapro is not recommended.

Warfarin

Administration of 40 mg/day racemic citalopram for 21 days did not affect the pharmacokinetics of warfarin, a CYP3A4 substrate. Prothrombin time was increased by 5%. The clinical significance of these findings is unknown.

13 NONCLINICAL TOXICOLOGY

13.1 Carcinogenesis, Mutagenesis, Impairment of Fertility

Carcinogenesis

Racemic citalopram was administered in the diet to NMRI/BOM strain mice and COBS WI strain rats for 18 and 24 months, respectively. There was no evidence for carcinogenicity of racemic citalopram in mice receiving up to 240 mg/kg/day. There was an increased incidence of small intestine carcinoma in rats receiving 8 or 24 mg/kg/day racemic citalopram. A no-effect dose for this finding was not established. The relevance of these findings to humans is unknown.

Mutagenesis

Racemic citalopram was mutagenic in the in vitro bacterial reverse mutation assay (Ames test) in 2 of 5 bacterial strains (Salmonella TA98 and TA1537) in the absence of metabolic activation. It was clastogenic in the in vitro Chinese hamster lung cell assay for chromosomal aberrations in the presence and absence of metabolic activation. Racemic citalopram was not mutagenic in the in vitro mammalian forward gene mutation assay (HPRT) in mouse lymphoma cells or in a coupled in vitro/in vivo unscheduled DNA synthesis (UDS) assay in rat liver. It was not clastogenic in the in vitro chromosomal aberration assay in human lymphocytes or in two in vivo mouse micronucleus assays.

Impairment of Fertility

When racemic citalopram was administered orally to 16 male and 24 female rats prior to and throughout mating and gestation at doses of 32, 48, and 72 mg/kg/day, mating was decreased at all doses, and fertility was decreased at doses ≥ 32 mg/kg/day. Gestation duration was increased at 48 mg/kg/day.

13.2 Animal Toxicology and/or Pharmacology

Retinal Changes in Rats

Pathologic changes (degeneration/atrophy) were observed in the retinas of albino rats in the 2-year carcinogenicity study with racemic citalopram. There was an increase in both incidence and severity of retinal pathology in both male and female rats receiving 80 mg/kg/day. Similar findings were not present in rats receiving 24 mg/kg/day of racemic citalopram for two years, in mice receiving up to 240 mg/kg/day of racemic citalopram for 18 months, or in dogs receiving up to 20 mg/kg/day of racemic citalopram for one year.

Additional studies to investigate the mechanism for this pathology have not been performed, and the potential significance of this effect in humans has not been established.

Cardiovascular Changes in Dogs

In a one-year toxicology study, 5 of 10 beagle dogs receiving oral racemic citalopram doses of 8 mg/kg/day died suddenly between weeks 17 and 31 following initiation of treatment. Sudden deaths were not observed in rats at doses of racemic citalopram up to 120 mg/kg/day, which produced plasma levels of citalopram and its metabolites demethylcitalopram and didemethylcitalopram (DDCT) similar to those observed in dogs at 8 mg/kg/day. A subsequent intravenous dosing study demonstrated that in beagle dogs, racemic DDCT caused QT prolongation, a known risk factor for the observed outcome in dogs.

14 CLINICAL STUDIES

14.1 Major Depressive Disorder

Adults
The efficacy of Lexapro as a treatment for major depressive disorder was established in three, 8-week, placebo-controlled studies conducted in outpatients between 18 and 65 years of age who met DSM-IV criteria for major depressive disorder. The primary outcome in all three studies was change from baseline to endpoint in the Montgomery Asberg Depression Rating Scale (MADRS).

A fixed-dose study compared 10 mg daily Lexapro and 20 mg daily Lexapro to placebo and 40 mg daily citalopram. The 10 mg daily and 20 mg daily Lexapro treatment groups showed statistically significant greater mean improvement compared to placebo on the MADRS. The 10 mg and 20 mg Lexapro groups were similar on this outcome measure.

In a second fixed-dose study of 10 mg daily Lexapro and placebo, the 10 mg daily Lexapro treatment group showed statistically significant greater mean improvement compared to placebo on the MADRS.

In a flexible-dose study, comparing Lexapro, titrated between 10 mg and 20 mg daily, to placebo and citalopram, titrated between 20 mg and 40 mg daily, the Lexapro treatment group showed statistically significant greater mean improvement compared to placebo on the MADRS.

Analyses of the relationship between treatment outcome and age, gender, and race did not suggest any differential responsiveness on the basis of these patient characteristics.

In a longer-term trial, 274 patients meeting (DSM-IV) criteria for major depressive disorder, who had responded during an initial 8 week, open-label treatment phase with Lexapro 10 mg or 20 mg daily, were randomized to continuation of Lexapro at their same dose, or to placebo, for up to 36 weeks of observation for relapse. Response during the open-label phase was defined by having a decrease of the MADRS total score to ≤ 12. Relapse during the double-blind phase was defined as an increase of the MADRS total score to ≥ 22, or discontinuation due to insufficient clinical response. Patients receiving continued Lexapro experienced a statistically significant longer time to relapse compared to those receiving placebo.

Pediatric Patients 12 years of age and older

The efficacy of Lexapro as a treatment for major depressive disorder in pediatric patients 12 to 17 years was established in an 8-week, flexible-dose, placebo-controlled study that compared Lexapro (10 mg to 20 mg daily) to placebo in outpatients 12 to 17 years of age inclusive who met DSM-IV criteria for major depressive disorder (MDD). The primary outcome was change from baseline to endpoint in the Children’s Depression Rating Scale - Revised (CDRS-R). In this study, Lexapro showed statistically significant greater mean improvement compared to placebo on the CDRS-R.

The efficacy of Lexapro in the treatment of major depressive disorder in pediatric patients 12 to 17 years was established, in part, on the basis of extrapolation from the 8-week, flexible-dose, placebo-controlled study with racemic citalopram 20 mg to 40 mg daily. In this outpatient study in pediatric patients 7 to 17 years of age who met DSM-IV criteria for major depressive disorder, citalopram treatment showed statistically significant greater mean improvement from baseline, compared to placebo, on the CDRS-R; the positive results for this trial largely came from the 12 to 17 year subgroup.

Two additional flexible-dose, placebo-controlled MDD studies (one Lexapro study in patients ages 7 to 17 years and one citalopram study patients 13 to 18 years) did not demonstrate efficacy. The safety and effectiveness of Lexapro have not been established in pediatric patients less than 12 years of age with MDD.

14.2 Generalized Anxiety Disorder

Adults

The efficacy of Lexapro in the treatment of generalized anxiety disorder (GAD) in adults was demonstrated in three, 8-week, multicenter, flexible-dose, placebo-controlled studies that compared Lexapro (10 mg to 20 mg daily) to placebo in outpatients between 18 and 80 years of age who met DSM-IV criteria for GAD. In all three studies, Lexapro showed statistically significant greater mean improvement compared to placebo on the Hamilton Anxiety Scale (HAM-A).

There were too few patients in differing ethnic and age groups to adequately assess whether or not Lexapro has differential effects in these groups. There was no difference in response to Lexapro between men and women.

Pediatric Patients 7 years of age and older

The efficacy of Lexapro in the treatment for generalized anxiety disorder (GAD) in pediatric patients 7 to 17 years was established in an 8-week, flexible-dose, placebo-controlled study that compared Lexapro (10 mg to 20 mg daily) to placebo in outpatients 7 to 17 years of age who met DSM-V criteria for GAD. The primary outcome was change from baseline to Week 8 in the Pediatric Anxiety Rating Scale (PARS) severity score for GAD. In this study, Lexapro showed a statistically significant treatment difference when compared to placebo on the PARS severity score for GAD (Least squares mean difference: −1.42, 95% confidence interval [−2.69, −0.15]).

16 HOW SUPPLIED/STORAGE AND HANDLING

How Supplied

Tablets

5 mg Tablets:

Bottle of 100 NDC # 0456-2005-01

White to off-white, round, non-scored, film-coated. Imprint "FL" on one side of the tablet and "5" on the other side.

10 mg Tablets:

Bottle of 100 NDC # 0456-2010-01

10 x 10 Unit Dose NDC # 0456-2010-63

White to off-white, round, scored, film-coated. Imprint on scored side with "F" on the left side and "L" on the right side. Imprint on the non-scored side with "10".

20 mg Tablets:

Bottle of 100 NDC # 0456-2020-01

10 x 10 Unit Dose NDC # 0456-2020-63

White to off-white, round, scored, film-coated. Imprint on scored side with "F" on the left side and "L" on the right side. Imprint on the non-scored side with "20".

Oral Solution

5 mg/5 mL, peppermint flavor (240 mL) NDC # 0456-2101-08. The oral solution is not currently being marketed.

Storage and Handling

Store at 20°C to 25°C (68°F to 77°F); excursions permitted to 15 to 30°C (59° to 86°F).

17 PATIENT COUNSELING INFORMATION

Advise the patient to read the FDA-approved patient labeling (Medication Guide).

Suicidal Thoughts and Behaviors

Advise patients, their families and caregivers to look for the emergence of suicidal ideation and behavior, especially during treatment and when the dose is adjusted up or down, and instruct them to report such symptoms to their healthcare provider [see Boxed Warning and Warnings and Precautions (5.1)].

Serotonin Syndrome
Caution patients about the risk of serotonin syndrome, particularly with the with the concomitant use of Lexapro with other serotonergic drugs including triptans, tricyclic antidepressants, opioids, lithium, tryptophan, buspirone, amphetamines, and St. John’s Wort, and with drugs that impair metabolism of serotonin (in particular, MAOIs, both those intended to treat psychiatric disorders and also others, such as linezolid). Instruct patients to contact their health care provider or report to the emergency room if they experience signs or symptoms of serotonin syndrome [see Warnings and Precautions (5.2), Drug Interactions (7)].

Discontinuation Syndrome

Advise patients not to abruptly discontinue Lexapro and to discuss any tapering regimen with their healthcare provider. Inform patients that adverse reactions can occur when Lexapro is discontinued [see Warnings and Precautions (5.3)].

Activation of Mania or Hypomania
Advise patients and their caregivers to observe for signs of activation of mania/hypomania and instruct them to report such symptoms to the healthcare provider [see Warnings and Precautions (5.5)].

Increased Risk of Bleeding

Inform patients about the concomitant use of Lexapro with NSAIDs, aspirin, warfarin, other antiplatelet drugs, or other anticoagulants because the combined use has been associated with an increased risk of bleeding. Advise patients to inform their healthcare providers if they are taking or planning to take any prescription or over-the-counter medications that increase the risk of bleeding [see Warnings and Precautions (5.7)].

Angle Closure Glaucoma
Advise patients that taking Lexapro can cause mild pupillary dilation, which in susceptible individuals, can lead to an episode of angle closure glaucoma. Pre-existing glaucoma is almost always open-angle glaucoma because angle closure glaucoma, when diagnosed, can be treated definitively with iridectomy. Open-angle glaucoma is not a risk factor for angle closure glaucoma. Patients may wish to be examined to determine whether they are susceptible to angle closure, and have a prophylactic procedure (e.g., iridectomy), if they are susceptible [see Warnings and Precautions (5.9)].

Sexual Dysfunction
Advise patients that use of Lexapro may cause symptoms of sexual dysfunction in both male and female patients. Inform patients that they should discuss any changes in sexual function and potential management strategies with their healthcare provider [see Warnings and Precautions (5.11)].

Concomitant Medications
Since escitalopram is the active isomer of racemic citalopram (Celexa), the two agents should not be coadministered. Patients should be advised to inform their physician if they are taking, or plan to take, any prescription or over-the-counter drugs, as there is a potential for interactions.

Interference with Psychomotor Performance
Because psychoactive drugs may impair judgment, thinking, or motor skills, patients should be cautioned about operating hazardous machinery, including automobiles, until they are reasonably certain that Lexapro therapy does not affect their ability to engage in such activities.

Alcohol
Patients should be told that, although Lexapro has not been shown in experiments with normal subjects to increase the mental and motor skill impairments caused by alcohol, the concomitant use of Lexapro and alcohol in depressed patients is not advised.

Pregnancy
Advise pregnant women to notify their healthcare providers if they become pregnant or intend to become pregnant during treatment with LEXAPRO.

Advise patients that LEXAPRO use later in pregnancy may lead to increased risk for neonatal complications requiring prolonged hospitalization, respiratory support, tube feeding, and/or persistent pulmonary hypertension (PPHN) of the newborn [see Use in Specific Populations (8.1)].

Advise women that there is a pregnancy exposure registry that monitors pregnancy outcomes in women exposed to LEXAPRO during pregnancy [see Use in Specific Populations (8.1)].

Lactation
Advise breastfeeding women using LEXAPRO to monitor infants for excess sedation, restlessness, agitation, poor feeding and poor weight gain and to seek medical care if they notice these signs [see Use in Specific Populations (8.2)].

Distributed by:
Abbvie Inc.
1 N Waukegan Rd.
North Chicago, IL 60064

Licensed from H. Lundbeck A/S
©2023 AbbVie. All rights reserved.
LEXAPRO and its design are trademarks of H. Lundbeck A/S, used under license by AbbVie.
20085417

MEDICATION GUIDE
Lexapro® (leks-a-pro)
(escitalopram)
tablets
oral solution

What is the most important information I should know about Lexapro?
Lexapro may cause serious side effects, including:

- Increased risk of suicidal thoughts or actions. Lexapro and other antidepressant medicines increase the risk of suicidal thoughts and actions in people 24 years of age and younger, especially within the first few months of treatment or when the dose is changed.
  ○ Depression or other mental illnesses are the most important causes of suicidal thoughts or actions.
  How can I watch for and try to prevent suicidal thoughts and actions?
  ○ Pay close attention to any changes, especially sudden changes in mood, behavior, thoughts, or feelings, or if you or your child develop suicidal thoughts or actions. This is very important when an antidepressant medicine is started or when the dose is changed.
  ○ Call your healthcare provider right away to report new or sudden changes in mood, behavior, thoughts, or feelings or if you or your child develop suicidal thoughts or actions.
  ○ Keep all follow-up visits with your healthcare provider as scheduled and call your healthcare provider between visits if you are worried about symptoms.

Call your healthcare provider or get emergency medical help right away if you or your child have any of the following symptoms, especially if they are new, worse, or worry you:

- attempts to commit suicide

- acting on dangerous impulses

- acting aggressive, being angry or violent

- thoughts about suicide or dying

- new or worse depression

- new or worsening anxiety

- panic attacks

- feeling very agitated or restless

- new or worse irritability

- trouble sleeping

- an extreme increase in activity or talking (mania)

- other unusual changes in behavior or mood

What is Lexapro?
Lexapro is a prescription medicine used to treat:

- a certain type of depression called Major Depressive Disorder (MDD) in adults and children 12 years of age and older
- Generalized Anxiety Disorder (GAD) in adults and children 7 years of age and older

It is not known if Lexapro is safe and effective for use in children under 12 years of age with MDD or children under 7 years of age with GAD.

Do not take Lexapro if you or your child:

- are taking, or have stopped taking within the last 14 days, a medicine called a monoamine oxidase inhibitor (MAOI), including the antibiotic linezolid or intravenous methylene blue
- are taking the antipsychotic medicine pimozide
- are allergic to escitalopram or citalopram or any of the ingredients in Lexapro. See the end of this Medication Guide for a complete list of ingredients in Lexapro.

Ask your healthcare provider or pharmacist if you are not sure if you or your child take an MAOI, including the antibiotic linezolid or intravenous methylene blue.
Do not start taking an MAOI for at least 14 days after you or your child have stopped treatment with Lexapro.

Before taking Lexapro, tell your healthcare provider about all your medical conditions, including if you or your child:

- have or had seizures or convulsions
- have, or have a family history of bipolar disorder, mania, or hypomania
- have low blood sodium levels
- have or had bleeding problems
- have high pressure in the eye (glaucoma)
- have heart, liver, or kidney problems
- are pregnant or plan to become pregnant. Lexapro may harm the unborn baby. Taking Lexapro during the third trimester of pregnancy may cause the baby to have withdrawal symptoms, or breathing, temperature control, feeding, or other problems after birth. Talk to your healthcare provider about the risks to the baby if you or your child take Lexapro during pregnancy.
  ○ Tell your healthcare provider right away if you or your child become pregnant or think you may be pregnant during treatment with Lexapro.
  ○ There is a pregnancy registry for females who are exposed to Lexapro during pregnancy. The purpose of the registry is to collect information about the health of females exposed to Lexapro and their baby. If you or your child become pregnant during treatment with Lexapro, talk to your healthcare provider about registering with the National Pregnancy Registry for Antidepressants at 1-844-405-6185 or visit online at https://womensmentalhealth.org/research/pregnancyregistry/antidepressants.
- are breastfeeding or plan to breastfeed. Lexapro passes into breast milk and may harm the baby. Talk to your healthcare provider about the best way to feed the baby during treatment with Lexapro.
  ○ If you or your child breastfeed during treatment with Lexapro, call your healthcare provider if the baby develops sleepiness or fussiness, or is not feeding or gaining weight well.

Tell your healthcare provider about all the medicines you or your child take, including prescription and non-prescription medicines, vitamins, and herbal supplements.
Lexapro and some medicines may affect each other and may cause serious side effects.
Lexapro may affect the way other medicines work and other medicines may affect the way Lexapro works.
Especially tell your healthcare provider if you take:

- medicines used to treat migraine headache known as triptans
- tricyclic antidepressants
- lithium
- tramadol, fentanyl, meperidine, methadone, or other opioids
- tryptophan
- buspirone
- amphetamines
- St. John’s Wort
- medicines used to treat mood, anxiety, psychotic or thought disorders, including selective serotonin reuptake inhibitors (SSRIs) and serotonin norepinephrine reuptake inhibitors (SNRIs)
- diuretics
- medicines that can affect blood clotting such as aspirin, nonsteroidal anti-inflammatory drugs (NSAIDs) and warfarin

Ask your healthcare provider if you are not sure if you or your child are taking any of these medicines. Your healthcare provider can tell you if it is safe to take Lexapro with your other medicines.
Do not start or stop any other medicines during treatment with Lexapro without talking to your healthcare provider first. Stopping Lexapro suddenly may cause you or your child to have serious side effects. See, “What are the possible side effects of Lexapro?”
Know the medicines you or your child take. Keep a list of them to show your healthcare provider and pharmacist when you get new medicine.

How should I take Lexapro?

- Take Lexapro exactly as prescribed. Your healthcare provider may need to change the dose of Lexapro until it is the right dose for you or your child.
- Take Lexapro 1 time each day, in the morning or the evening.
- Take Lexapro with or without food.
- If you or your child take too much Lexapro, call your healthcare provider or Poison Help Line at 1-800-222-1222, or go to the nearest hospital emergency room right away.

What should I avoid while taking Lexapro?

- Do not drive, operate heavy machinery, or do other dangerous activities until you know how Lexapro affects you. Lexapro can cause sleepiness or may affect your ability to make decisions, think clearly, or react quickly.
- Do not drink alcohol during treatment with Lexapro.

What are the possible side effects of Lexapro?
Lexapro may cause serious side effects, including:

- See “What is the most important information I should know about Lexapro?”
- Serotonin syndrome. A potentially life-threatening problem called serotonin syndrome can happen when Lexapro is taken with certain other medicines. See “Do not take Lexapro if you?” Call your healthcare provider or go to the nearest hospital emergency room right away if you or your child have any of the following signs and symptoms of serotonin syndrome:

- agitation

- seeing or hearing things that are not real (hallucinations)

- confusion

- coma

- fast heartbeat

- blood pressure changes

- sweating

- shaking (tremors), stiff muscles, or muscle twitching

- flushing

- dizziness

- seizures

- high body temperature (hyperthermia)

- nausea, vomiting, diarrhea

- loss of coordination

- Discontinuation syndrome. Suddenly stopping Lexapro may cause you or your child to have serious side effects. Your healthcare provider may want to decrease the dose slowly. Symptoms may include:

- changes in mood

- headache

- irritability and agitation

- tiredness

- dizziness

- problems sleeping

- electric shock sensation (paresthesia)

- hypomania

- anxiety

- ringing in your ears (tinnitus)

- confusion

- seizures

- Seizures (convulsions).

- Manic episodes. Manic episodes may happen in people with bipolar disorder who take Lexapro. Symptoms may include:

- greatly increased energy

- severe trouble sleeping

- racing thoughts

- reckless behavior

- unusually grand ideas

- excessive happiness or irritability

- talking more or faster than usual

- Low sodium levels in the blood (hyponatremia). Low sodium levels in the blood that may be serious and may cause death can happen during treatment with Lexapro. Elderly people and people who take certain medicines may be at greater risk for developing low sodium levels in the blood. Signs and symptoms may include:

- headache

- problems concentrating or thinking

- weakness or feeling unsteady which can lead to falls

- confusion

- memory problems

In more severe or more sudden cases, signs and symptoms include:

- seeing or hearing things that are not real (hallucinations)

- fainting

- seizures

- coma

- stopping breathing (respiratory arrest)

- Increased risk of bleeding: Taking Lexapro with aspirin, NSAIDS, warfarin, or other blood thinners may add to this risk. Tell your healthcare provider if you have any unusual bleeding or bruising.

- Visual problems (angle-closure glaucoma). Lexapro may cause a type of eye problem called angle-closure glaucoma in people with certain eye problems. You or your child may want to undergo an eye examination to see if you are at risk and receive preventative treatment if you are. Call your healthcare provider if you or your child have:

- eye pain

- changes in vision

- swelling or redness in or around the eye

- Sexual problems (dysfunction). Taking Lexapro may cause sexual problems.
  Symptoms in males may include:

- delayed ejaculation or inability to have an ejaculation

- decreased sex drive

- problems getting or keeping an erection

Symptoms in females may include:

- decreased sex drive

- delayed orgasm or inability to have an orgasm

Talk to your healthcare provider if you develop any changes in your sexual function or if you have any questions or concerns about sexual problems during treatment with Lexapro. There may be treatments your healthcare provider can suggest.

The most common side effects of Lexapro include:

- trouble sleeping

- sweating

- decreased sex drive

- delayed ejaculation
- nausea

- tiredness
- sleepiness

- delayed orgasm or inability to have an orgasm

Height and weight changes in children may happen during treatment with Lexapro. Your child’s height and weight should be monitored during treatment with LEXAPRO.
These are not all the possible side effects of Lexapro.
Call your doctor for medical advice about side effects. You may report side effects to FDA at 1-800-FDA-1088.

How should I store Lexapro?

- Store Lexapro at room temperature between 68°F to 77°F (20°C to 25°C).
- Keep Lexapro and all medicines out of the reach of children.

General information about the safe and effective use of Lexapro.
Medicines are sometimes prescribed for purposes other than those listed in a Medication Guide. Do not use Lexapro for a condition for which it was not prescribed. Do not give Lexapro to other people, even if they have the same symptoms that you have. It may harm them. You may ask your pharmacist or healthcare provider for information about Lexapro that is written for health professionals.

What are the ingredients in Lexapro?
Active ingredient: escitalopram oxalate
Inactive ingredients:
Tablets: talc, croscarmellose sodium, microcrystalline cellulose/colloidal silicon dioxide, and magnesium stearate. The film coating contains hypromellose, titanium dioxide, and polyethylene glycol
Oral solution: sorbitol, purified water, citric acid, sodium citrate, malic acid, glycerin, propylene glycol, methylparaben, propylparaben, and natural peppermint flavor
Distributed by:
AbbVie Inc.
1 N Waukegan Rd.
North Chicago, IL 60064
Licensed from H. Lundbeck A/S
©2024 AbbVie. All rights reserved.
LEXAPRO and its design are trademarks of H. Lundbeck A/S, used under license by AbbVie.
For more information about Lexapro, call 1-800-678-1605 or go to www.Lexapro.com

This Medication Guide has been approved by the U.S. Food and Drug Administration. Revised:4/2024

20085417

PRINCIPAL DISPLAY PANEL

NDC 0456-2005-01
Lexapro
escitalopram
Tablets 5 mg

Equivalent to 5 mg escitalopram
100 Tablets
Rx Only

PRINCIPAL DISPLAY PANEL

NDC 0456-2010-01
Lexapro
escitalopram
Tablets 10 mg

Equivalent to 10 mg escitalopram
100 Tablets
Rx Only

PRINCIPAL DISPLAY PANEL

NDC 0456-2020-01
Lexapro
escitalopram
Tablets 20 mg

Equivalent to 20 mg escitalopram
100 Tablets
Rx Only

PRINCIPAL DISPLAY PANEL

NDC 0456-2101-08
Lexapro
escitalopram
Oral Solution 5 mg/5mL

Equivalent to 1 mg escitalopram/mL
8 fl oz (240 mL)
Rx Only